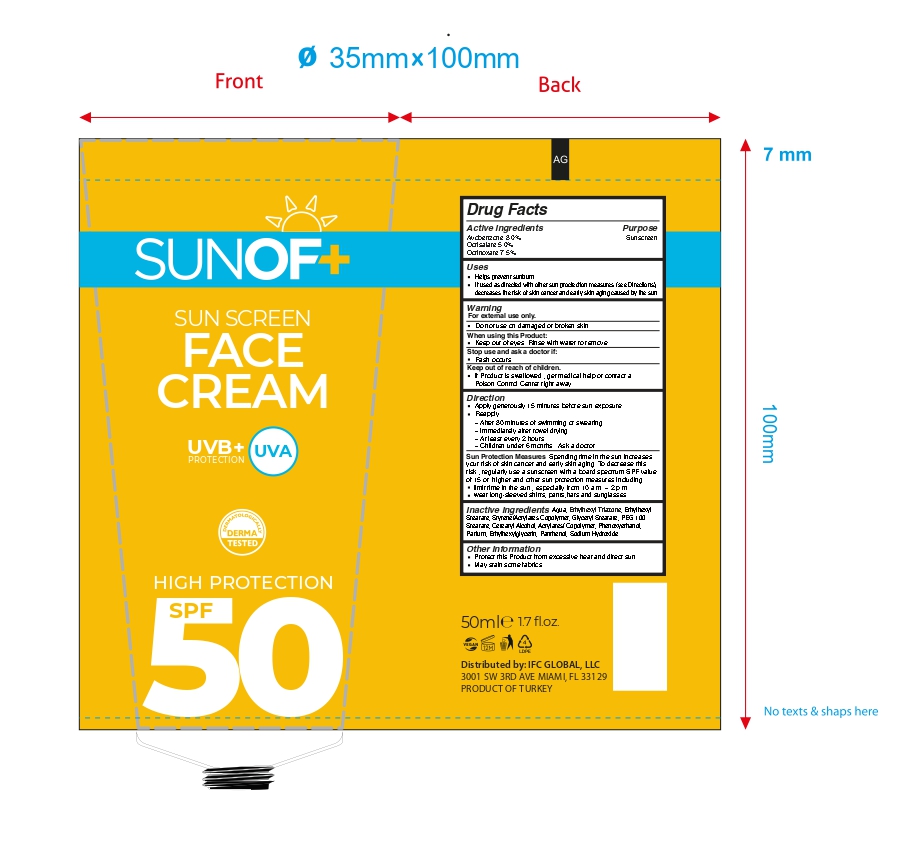 DRUG LABEL: SUNOF Sunscreen Face Cream SPF 50
NDC: 77418-005 | Form: CREAM
Manufacturer: ATAK FARMA KOZMETIK VE KIMYA SANAYI TICARET ANONIM SIRKETI
Category: otc | Type: HUMAN OTC DRUG LABEL
Date: 20250813

ACTIVE INGREDIENTS: AVOBENZONE 3 g/100 mL; OCTISALATE 5 g/100 mL; OCTINOXATE 7.5 g/100 mL
INACTIVE INGREDIENTS: ETHYLHEXYL STEARATE; ETHYLHEXYLGLYCERIN; AQUA; ETHYLHEXYL TRIAZONE; SODIUM HYDROXIDE; PHENOXYETHANOL; ACRYLIC ACID/2-ETHYLHEXYL ACRYLATE/STYRENE COPOLYMER (500000 MW); GLYCERYL STEARATE; PEG-100 STEARATE; CETEARYL ALCOHOL; PANTHENOL; PARFUMIDINE

Inactive Ingredients

Aqua , Ethylhexyl Triazone, Ethylhexyl Stearate ,Styrene/Acrylates Copolymer , Glyceryl Stearate , PEG-100 Stearate , Cetearyl Alcohol , Acrylates/ Copolymer , Phenoxyethanol ,Parfum , Ethylhexylglycerin ,Panthenol , Sodium Hydroxide.

Warnings

For external use only.

Do not use on damaged or broken skin.

When using this Product

Keep out of eyes.Rinse with water to remove.

Stop use and ask a doctor if rash occurs.

Active Ingredients

Avobenzone 3.0%

Octisalate 5.0%

Octinoxate 7.5%

Sun Protection Measures

Spending time in the sun increases

your risk of skin cancer and early skin aging. To decrease this

risk , regularly use a sunscreen with a board spectrum SPF value

of 15 or higher and other sun protection measures including:

limit time in the sun , especially from 10 a.m. – 2 p.m.

wear long-sleeved shirts, pants,hats and sunglasses.

Keep out of reach of children

If Product is swallowed , get medical help or contact a Poison Control Center right away.

Direction

Apply generously 15 minutes before sun exposure. reapply : after 80 minutes of swimming or sweating.Immediately after towel drying. At least every 2 hours . Children under 6 months : Ask a doctor. Sun Protection Measures . Spending time in the sun increases your risk of skin cancer and early skin aging. To decrease this risk , regularly use a sunscreen with a board spectrum SPF value of 15 or higher and other sun protection measures including: limit time in the sun , especially from 10 a.m. – 2 p.m. wear long-sleeved shirts, pants,hats and sunglasses.

Uses

Helps prevent sunburn

If used as directed with other sun proctection measures (see Directions), decreases the risk of skin cancer and early skin aging caused by the sun.

Purpose

Sunscreen